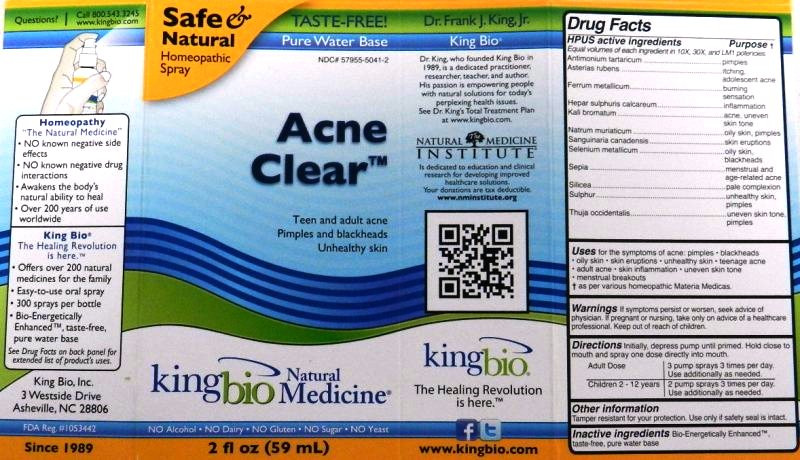 DRUG LABEL: Acne Clear
NDC: 57955-5041 | Form: LIQUID
Manufacturer: King Bio Inc.
Category: homeopathic | Type: HUMAN OTC DRUG LABEL
Date: 20111104

ACTIVE INGREDIENTS: ANTIMONY POTASSIUM TARTRATE 10 [hp_X]/59 mL; ASTERIAS RUBENS 10 [hp_X]/59 mL; IRON 10 [hp_X]/59 mL; CALCIUM SULFIDE 10 [hp_X]/59 mL; POTASSIUM BROMIDE 10 [hp_X]/59 mL; SODIUM CHLORIDE 10 [hp_X]/59 mL; SANGUINARIA CANADENSIS ROOT 10 [hp_X]/59 mL; SELENIUM 10 [hp_X]/59 mL; SEPIA OFFICINALIS JUICE 10 [hp_X]/59 mL; SILICON DIOXIDE 10 [hp_X]/59 mL; SULFUR 10 [hp_X]/59 mL; THUJA OCCIDENTALIS LEAFY TWIG 10 [hp_X]/59 mL
INACTIVE INGREDIENTS: WATER

Acne Clear

Active Ingredients

HPUS active ingredients
Equal volumes of each ingredient in 10X, 30X, and LM1 Potencies.
Antimonium tartaricum
Asterias rubens
Ferrum metallicum
Hepar sulphuris calcareum
Kali bromatum
Natrum muriaticum
Sanguinaria canadensis
Selenium metallicum
Sepia
Silicea
Sulphur
Thuja occidentalis
Reference image of acne.jpg

Inactive Ingredient

Bio-Energetically Enhanced, taste-free, pure water base.

Reference image of acne.jpg

Dosage and Administration

Directions: Initially, depress pump until primed. Hold close to mouth and spray one dose directly into mouth.

Adult Dose- 3 pump sprays 3 times per day. Use additionally as needed.

Children 2 - 12 years- 2 pump sprays 3 times per day. Use additionally as needed.

Reference image of acne.jpg

Purpose

HPUS active ingredients Purpose
Equal volumes of each ingredient in 10X, 30X, and LM1 Potencies.
Antimonium tartaricum..........................................pimples
Asterias rubens...................................................itching, adolescent acne
Ferrum metallicum...............................................burning sensation
Hepar sulphuris calcareum...................................inflammation
Kali bromatum.....................................................acne, uneven skin tone
Natrum muriaticum..............................................oily skin, pimples
Sanguinaria canadensis.......................................skin eruptions
Selenium metallicum............................................oily skin, blackheads
Sepia..................................................................menstrual and age-related acne
Silicea.................................................................pale complexion
Sulphur...............................................................unhealthy skin, pimples
Thuja occidentalis...............................................uneven skin tone, pimples
Reference image of acne.jpg

Indications and Usage

Uses for the symptoms of acne:

- pimples
- blackheads
- oily skin
- skin eruptions
- unhealthy skin
- teenage acne
- adult acne
- skin inflammation
- uneven skin tone
- menstrual breakouts

as per various homeopathic Materia Medicas.
King Bio Inc.
3 Westside Drive
Asheville, NC 28806
www.kingbio.com
Reference image of acne.jpg

Warnings

If symptoms persist or worsen, seek advice of physician. If pregnant or nursing, take only on advice of a healthcare professional. Keep out of reach of children.

Other information:

Tamper resistant for your protection. Use only if safety seal is intact.

Reference image of acne.jpg

Keep out of reach of children.

Reference image of acne.jpg

PACKAGE LABEL

Reference image of acne.jpg